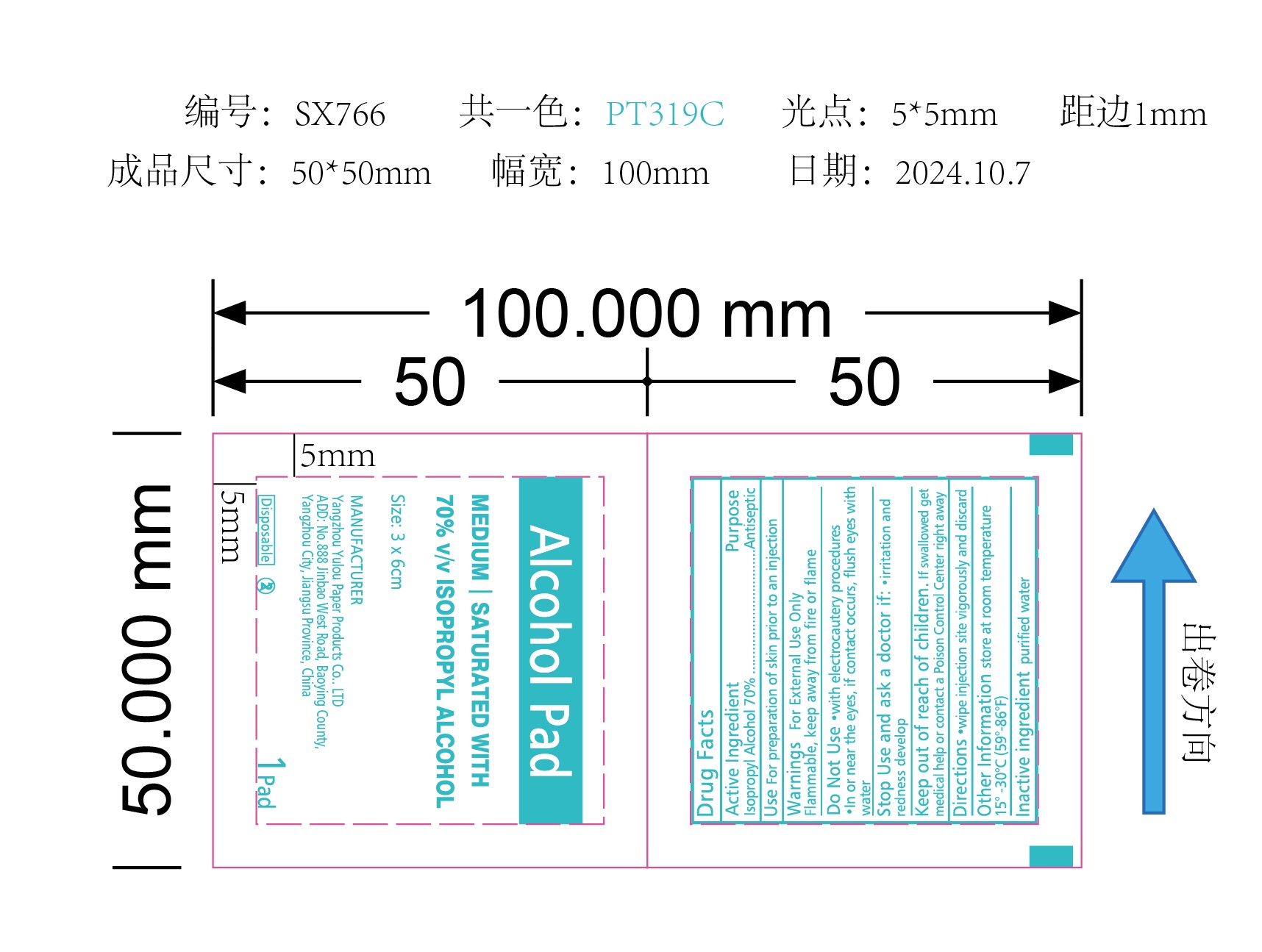 DRUG LABEL: Alcohol Pad
NDC: 84822-002 | Form: SWAB
Manufacturer: Yangzhou Yulou Paper Products Co., LTD
Category: otc | Type: HUMAN OTC DRUG LABEL
Date: 20241010

ACTIVE INGREDIENTS: ISOPROPYL ALCOHOL 0.7 mL/1 1
INACTIVE INGREDIENTS: WATER

Alcohol Pad

Active Ingredient

Isopropyl Alcohol, 70% v/v

Purpose

Antiseptic, Sterile Solution

Uses

Antiseptic cleanser

Kills harmful bacteria and germs

First aid to help prevent infection

Warnings

For External Use Only

Avoid contact with the eyes

If contact occurs, flush eyes with water

Do Not Use

With electrocautery prodedures

In the eyes

Stop Use and ask a doctor if

Irritation and redness develops

If condition persists for more than 72 hours, consult a physician

Discontinue use and consult a healthcare practitioner if

Irritation develops

Keep out of reach of children

If swallowed, get medical help or contact a Poison Control Center right away

Directions

Use as part of your daily cleansing routine

May be covered with a sterile bandage

Other Information

Store at room temperature 15°-30°C (59°-86°F)

Avoid excessive heat

Inactive Ingredients

Water